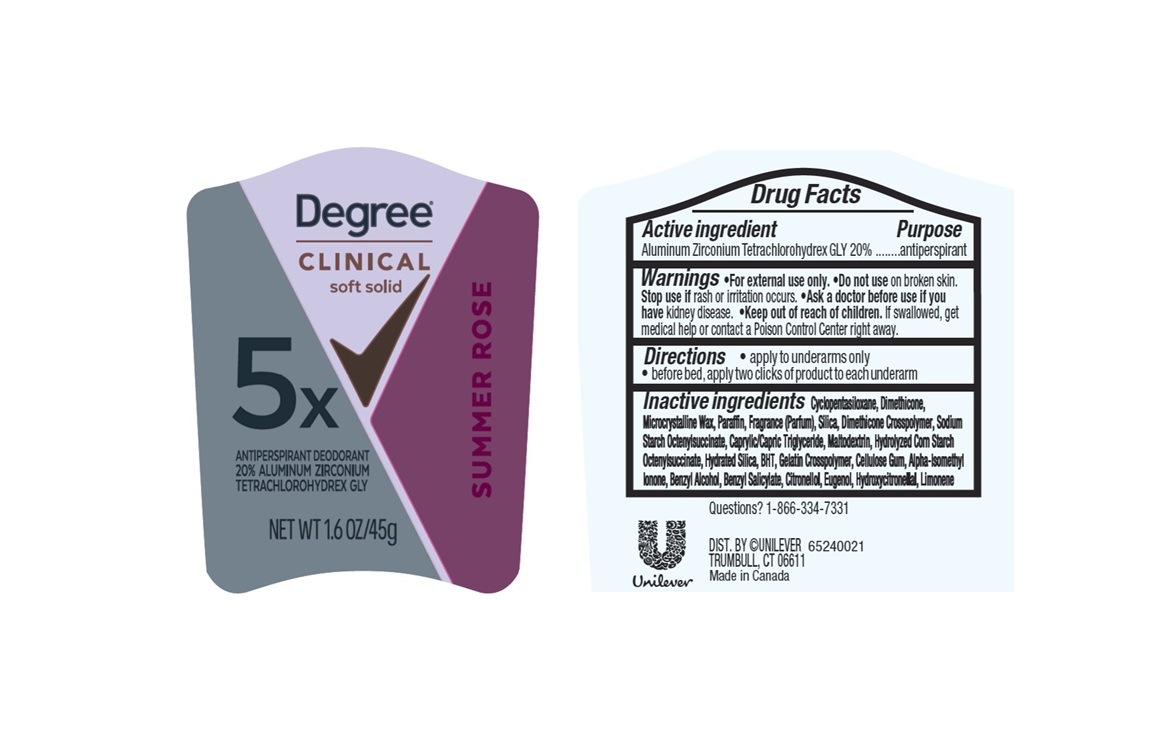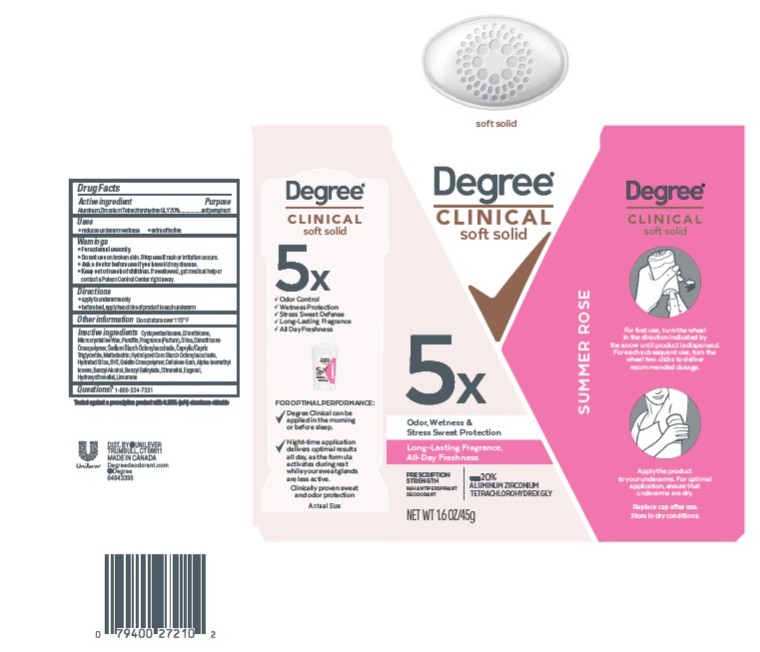 DRUG LABEL: Degree
NDC: 64942-2426 | Form: STICK
Manufacturer: Conopco d/b/a Unilever
Category: otc | Type: HUMAN OTC DRUG LABEL
Date: 20260226

ACTIVE INGREDIENTS: ALUMINUM ZIRCONIUM TETRACHLOROHYDREX GLY 20 g/100 g
INACTIVE INGREDIENTS: PARAFFIN; EUGENOL; DIMETHICONE; CAPRYLIC/CAPRIC TRIGLYCERIDE; MALTODEXTRIN; LIMONENE, (+)-; CITRONELLOL; CYCLOPENTASILOXANE; MICROCRYSTALLINE WAX; HYDROXYCITRONELLAL; DIMETHICONE CROSSPOLYMER; BHT; BENZYL ALCOHOL; SILICA; CELLULOSE GUM; BENZYL SALICYLATE; HYDRATED SILICA; ALPHA-ISOMETHYL IONONE

Degree Clinical Soft Solid Summer Rose Antiperspirant Deodorant

DESCRIPTION

Degree Clinical Soft Solid Summer Rose Antiperspirant Deodorant

ACTIVE INGREDIENT

Aluminum Zirconium Tetrachlorohydrex GLY 20%

PURPOSE

Antiperspirant

WARNINGS

For external use only • Do not use on broken skin. Stop use if rash or irritation occurs. • Ask a doctor before use if you have kidney disease. If swallowed, get medical help or contact a Poison Control Center right away

• Keep out of reach of children.

DOSAGE AND ADMINISTRATION

•apply to underarms only •before bed, apply two clicks of product to each underarm

INDICATIONS AND USAGE

• reduces underarm wetness • extra effective

OTHER SAFETY INFORMATION

Do not store over 115° F

INACTIVE INGREDIENT

Cyclopentasiloxane, Dimethicone, Microcrystalline Wax, Paraffin, Fragrance (Parfum), Silica, Dimethicone Crosspolymer, Sodium Starch Octenylsuccinate, Caprylic/Capric Triglyceride, Maltodextrin, Hydrolyzed Corn Starch Octenylsuccinate, Hydrated Silica, BHT, Gelatin Crosspolymer, Cellulose Gum, Alpha-Isomethyl Ionone, Benzyl Alcohol, Benzyl Salicylate, Citronellol, Eugenol, Hydroxycitronellal, Limonene

QUESTIONS

1-866-334-7331